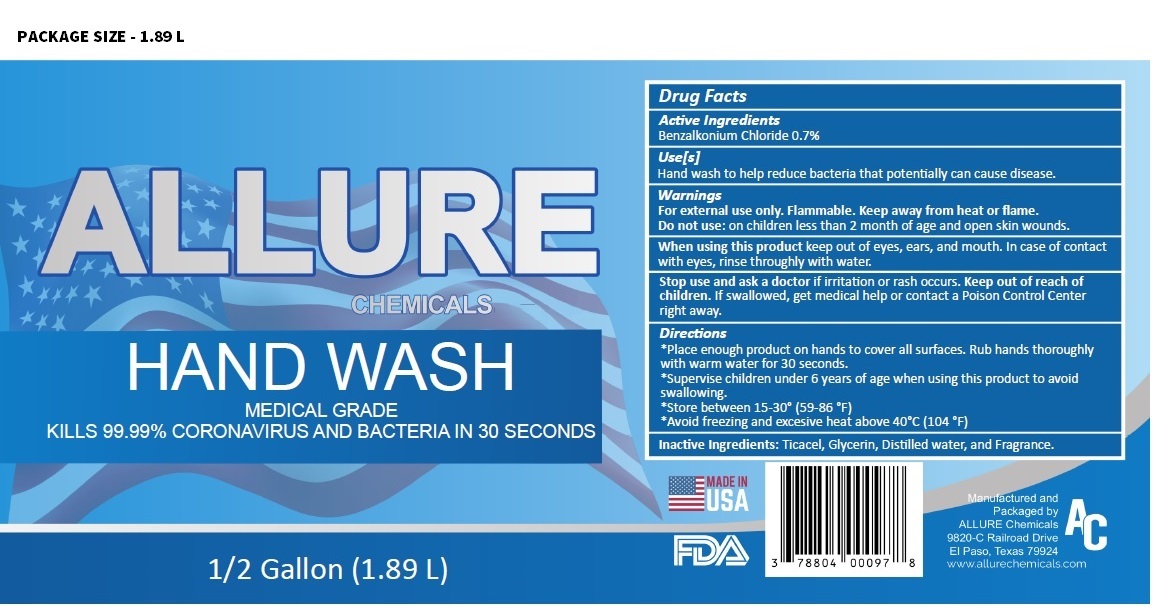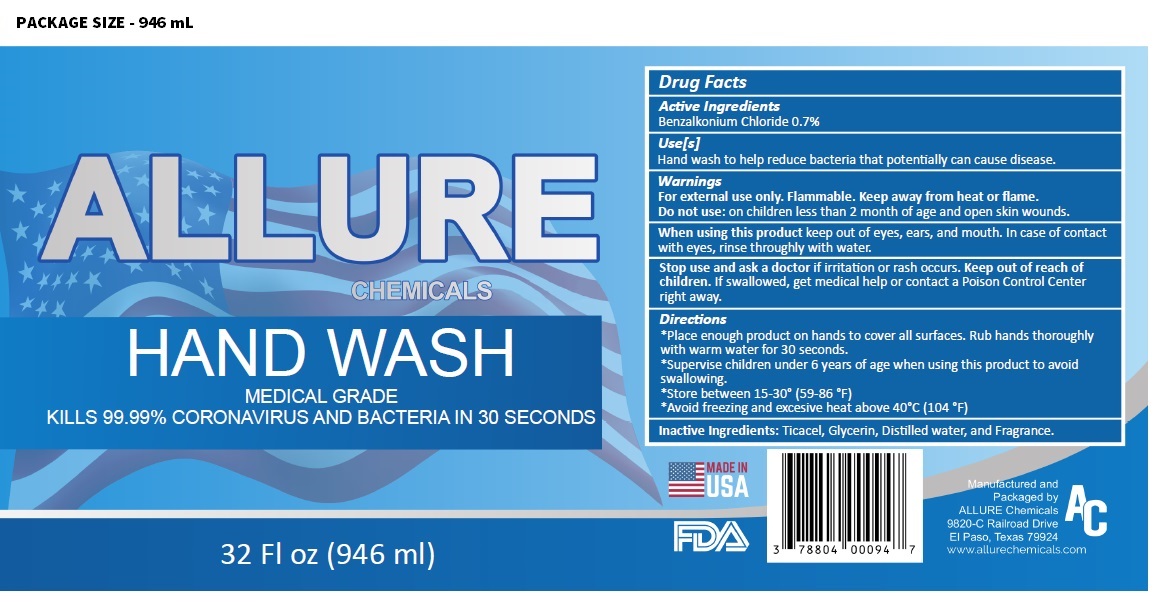 DRUG LABEL: ALLURE CHEMICALS HAND WASH
NDC: 78804-000 | Form: LIQUID
Manufacturer: Allure Chemicals LP
Category: otc | Type: HUMAN OTC DRUG LABEL
Date: 20210218

ACTIVE INGREDIENTS: BENZALKONIUM CHLORIDE 0.7 g/100 mL
INACTIVE INGREDIENTS: GLYCERIN; WATER

ALLURE CHEMICALS HAND WASH

Active Ingredients

Benzalkonium Chloride 0.7%

Purpose

Antibacterial

Use[s]

Hand wash to help reduce bacteria that potentially can cause disease.

Warnings

For external use only. Flammable. Keep away from heat or flame.

Do not use: on children less than 2 month of age and open skin wounds.

When using this product keep out of eyes, ears, and mouth. In case of contact with eyes, rinse thoroughly with water.

Stop use and ask a doctor if irritation or rash occurs.

Keep out of reach of children. If swallowed, get medical help or contact a Poison Control Center right away.

Directions

*Place enough product on hands to cover all surfaces. Rub hands thoroughly with warm water for 30 seconds.

*Supervise children under 6 years of age when using this product to avoid swallowing.

*Store between 15-30° (59-86 °F)

*Avoid freezing and excessive heat above 40°C (104 °F)

Inactive Ingredients:

Ticacel, Glycerin, Distilled water, and Fragrance.

MEDICAL GRADE

KILLS 99.99% CORONAVIRUS AND BACTERIA IN 30 SECONDS

Manufactured and Packaged by

ALLURE Chemicals

9820-C Railroad Drive

EI Paso, Texas 79924

www.allurechemicals.com

MADE IN USA